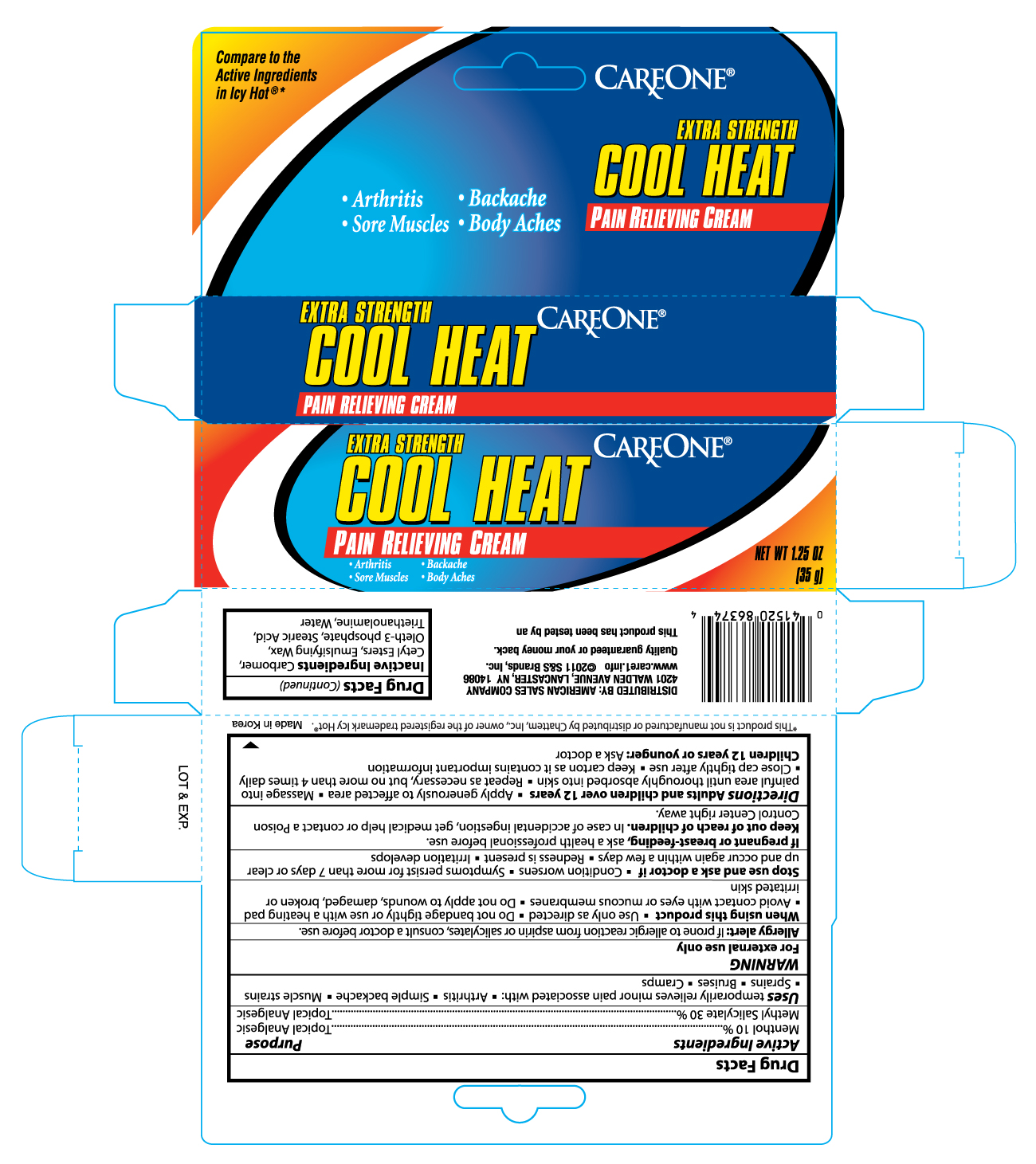 DRUG LABEL: CARE ONE COOL HEAT PAIN RELIEVING
NDC: 41520-863 | Form: CREAM
Manufacturer: AMERICAN SALES COMPANY
Category: otc | Type: HUMAN OTC DRUG LABEL
Date: 20120301

ACTIVE INGREDIENTS: MENTHOL 10 g/100 g; METHYL SALICYLATE 30 g/100 g
INACTIVE INGREDIENTS: CETYL ESTERS WAX; OLETH-3 PHOSPHATE; STEARIC ACID; TROLAMINE; WATER

Drug Facts

Active ingredients Purpose

Menthol 10%............................................................................................Topical Analgesic

Methyl Salicylate 30%...............................................................................Topical Analgesic

Uses

temporarily relieves minor pain associated with

- Arthritis
- Simple backache
- Muscle strains
- Sprains
- Bruises
- Cramps

Warning

For external use only

Allergy alert: If prone to allergic reaction from aspirin or salicylates, consult a doctor before use.

When using this product

- Use only as directed
- Do not bandage tightly or sue with a heating pad
- Avoid contact with eyes or mucous membranes
- Do not apply to wounds, damaged, broken or irritated skin

Stop use and ask a doctor if

- condition worsens
- symptoms persist for more than 7 days or clear up and occur again within a few days
- redness is present
- irritation develops

PREGNANCY OR BREAST FEEDING

If pregnant or breast-feeding, ask a health professional before use.

Keep out of reach of children. In case of accidental ingestion, get medical help or contact a Poison Control Center right away.

INDICATIONS AND USAGE

Directions Adults and children over 12 years

- apply generously to affected area
- massage into painful area until thoroughly absorbed into skin
- repeat as necessary but no more than 4 times daily
- close cap tightly after use
- keep carton as it contains important information

Children 12 years or younger: Ask a doctor

Inactive ingredients

Carbomer, Cetyl Esters, Emulsifying Wax, Oleth-3 phosphate, Stearic Acid, Triethanolamine, Water

DOSAGE AND ADMINISTRATION

DISTRIBUTED BY: AMERICAN SALES COMPANY

4201 WALDEN AVENUE, LANCASTER, NY 14086

www.care1.info

Made in Korea

PACKAGE LABEL

Enter section text here